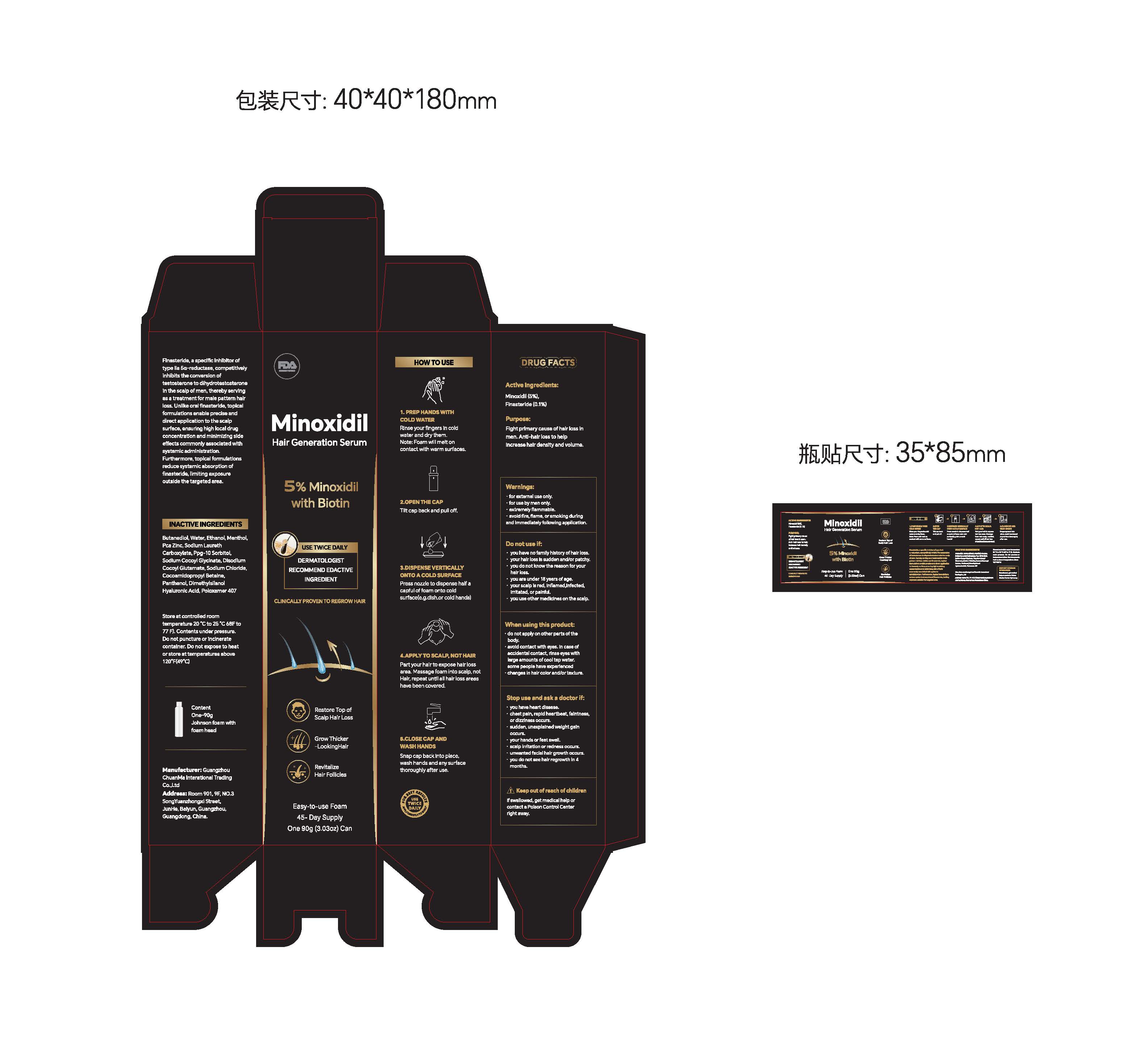 DRUG LABEL: Minoxidil Hair Generation Serum
NDC: 85593-020 | Form: PASTE
Manufacturer: Guangzhou ChuanMa International Trading Co.,Ltd.
Category: otc | Type: HUMAN OTC DRUG LABEL
Date: 20251215

ACTIVE INGREDIENTS: FINASTERIDE 0.1 g/100 g; MINOXIDIL 5 g/100 g
INACTIVE INGREDIENTS: 1,4-BUTANEDIOL; COCAMIDOPROPYL BETAINE; DIMETHYLSILANOL HYALURONATE; SODIUM CHLORIDE; ZINC PCA; WATER; ALCOHOL; MENTHOL, (+)-; SODIUM LAURETH-5 CARBOXYLATE; SODIUM COCOYL GLYCINATE; DISODIUM COCOYL GLUTAMATE; SORBITOL; POLOXAMER 407; PANTHENOL

Active Ingredients:Minoxidil (5%),Finasteride(0.1%)

KEEP OUT OF REACH OF CHILDREN

Keep out of reach of childrerIf swallowed, get medical help orcontact a Poison Control Centerright away.

PURPOSE

Purpose:Fight primary cause of hair loss inmen. Anti-hair loss to helpincrease hair density and volume.

Warnings:
for external use only.for use by men only.extremelyflammable.avoid fire, flame, or smoking duringand immediately following application.

INDICATIONS AND USAGE

1. PREP HANDS WITH
COLD WATER
Rinse your fingers in cold
water and dry them.
Note: Foam will melt on
contact with warm surfaces
2.OPEN THE CAP
Tilt cap back and pull off.
3.DISPENSE VERTICALLY
ONTO A COLD SURFACE
Press nozzle to dispense half acapful of foam onto cold
surface(e.g.dish.or cold hands)
4.APPLY TO SCALP, NOT HAIR
Part your hair to expose hair lossarea.Massage foam into scalp, notHair, repeat until all hair loss areashave been covered.
5.CLOSE CAP AND
WASH HANDS
Snap cap back into place,
wash hands and any surface
thoroughly after use.

DOSAGE AND ADMINISTRATION

Take an appropriate amount and place it in the palm

INACTIVE INGREDIENT

Butanediol, Water, Ethanol, Menthol.Pca Zinc, Sodium LaurethCarboxylate, Ppg-10 Sorbitol,Sodium Cocoyl Glycinate, DisodiumCocoyl Glutamate, Sodium Chloride,Cocoamidopropyl Betaine,Panthenol, DimethylsilanolHyaluronic Acid, Poloxamer 407